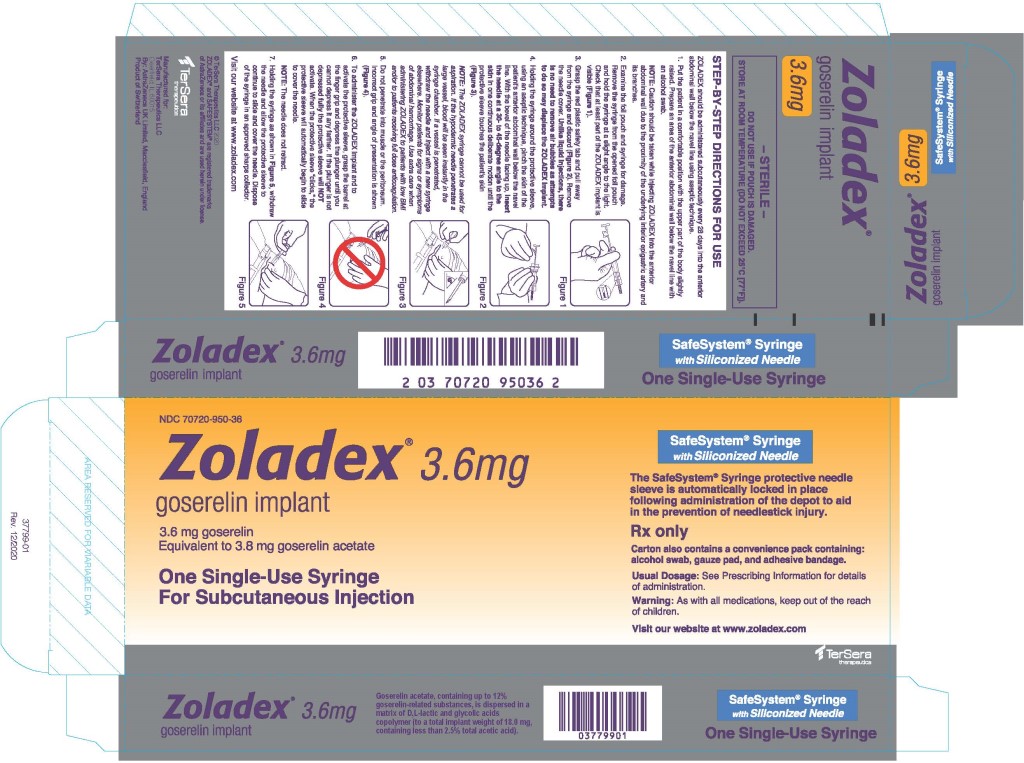 DRUG LABEL: ZOLADEX
NDC: 70720-950 | Form: IMPLANT
Manufacturer: TerSera Therapeutics LLC
Category: prescription | Type: HUMAN PRESCRIPTION DRUG LABEL
Date: 20250924

ACTIVE INGREDIENTS: goserelin acetate 3.6 mg/1 1
INACTIVE INGREDIENTS: Glycolic Acid; Lactic Acid, DL-

HIGHLIGHTS OF PRESCRIBING INFORMATION

These highlights do not include all the information needed to use ZOLADEX safely and effectively.
See full prescribing information for ZOLADEX.
ZOLADEX® (goserelin implant) 3.6 mg
Initial U.S. Approval: 1989

RECENT MAJOR CHANGES

Warnings and Precautions (5.7) | 9/2025

1 INDICATIONS AND USAGE

ZOLADEX is a Gonadotropin Releasing Hormone (GnRH) agonist indicated for:

- Use in combination with flutamide for the management of locally confined carcinoma of the prostate (1.1)
- Palliative treatment of advanced carcinoma of the prostate (1.2)
- The management of endometriosis (1.3)
- Use as an endometrial-thinning agent prior to endometrial ablation for dysfunctional uterine bleeding (1.4)
- Use in the palliative treatment of advanced breast cancer in pre- and perimenopausal women (1.5)

2 DOSAGE AND ADMINISTRATION

- ZOLADEX 3.6 mg should be administered subcutaneously every 28 days (2.1, 2.7)
- For the management of endometriosis, the recommended duration of administration is 6 months for women 18 years of age and older (2.3)

3 DOSAGE FORMS AND STRENGTHS

Implant 3.6 mg (3)

4 CONTRAINDICATIONS

- Hypersensitivity (4.1)
- Pregnancy unless used for treatment of advanced breast cancer (4.2)

5 WARNINGS AND PRECAUTIONS

- Women of Childbearing Potential and Pregnancy: Pregnancy must be excluded for use in benign gynecological conditions. Women should avoid pregnancy (5.1)
- Tumor Flare Phenomenon: Transient worsening of tumor symptoms may occur during the first few weeks of treatment with ZOLADEX, which may include ureteral obstruction and spinal cord compression. Monitor patients at risk for complications of tumor flare (5.2, 6.2)
- Hyperglycemia and Diabetes: Hyperglycemia and an increased risk of developing diabetes have been reported in men receiving GnRH analogs. Monitor blood glucose level and manage according to current clinical practice (5.3)
- Cardiovascular Diseases: Increased risk of myocardial infarction, sudden cardiac death and stroke has been reported in association with use of GnRH analogs in men. Monitor for cardiovascular disease and manage according to current clinical practice (5.4)
- Hypercalcemia: Hypercalcemia has been reported in patients with bone metastases treated with ZOLADEX. Monitor and manage appropriately (5.5)
- Hypersensitivity: Systemic hypersensitivity has been reported in patients receiving goserelin/ZOLADEX implants (4.1, 5.6)
- Severe Cutaneous Adverse Reactions: ZOLADEX can cause severe cutaneous adverse reactions (SCARs), including Stevens-Johnson syndrome/toxic epidermal necrolysis. Interrupt ZOLADEX if signs or symptoms of SCARs develop. Permanently discontinue ZOLADEX if SCARs are confirmed. (5.7)
- Cervical Resistance: Increase in cervical resistance may occur. Caution is recommended when dilating the cervix for endometrial ablation (5.8)
- Effect on QT/QTc Interval: Androgen deprivation therapy may prolong the QT interval. Consider risks and benefits (5.9)
- Injection Site Injury: Injection site injury and vascular injury have been reported during administration of ZOLADEX (5.10)
- Depression: Depression may occur or worsen in women receiving GnRH agonists. Monitor and manage appropriately (5.11)

6 ADVERSE REACTIONS

The most common, clinically significant adverse reactions occurring in >10% of men: hot flashes, sexual dysfunction, decreased erections and lower urinary tract symptoms (6)

The adverse event profile was similar for women treated for breast cancer, dysfunctional uterine bleeding or endometriosis and included (>20%): hot flushes, headache, sweating, acne, emotional lability, depression, decreased libido, vaginitis, breast atrophy, seborrhea, and peripheral edema (6)

Tumor flare can occur on the initiation of ZOLADEX for both men and women being treated for cancer (6)

To report SUSPECTED ADVERSE REACTIONS, contact TerSera Therapeutics at 1-844-334-4035 or FDA at 1-800-FDA-1088 or www.fda.gov/medwatch.

7 DRUG INTERACTIONS

- None

8 USE IN SPECIFIC POPULATIONS

- Nursing mothers: Discontinue drug or nursing taking into account the importance of drug to the mother (8.3)
- No information available for use in Pediatric patients (8.4)
- Geriatric (8.5)
- Renal and Hepatic Impairment: No dose adjustment is necessary (2.6, 8.6, 8.7)

FULL PRESCRIBING INFORMATION

1 INDICATIONS AND USAGE

1.1 Stage B2-C Prostatic Carcinoma

ZOLADEX is indicated for use in combination with flutamide for the management of locally confined Stage T2b-T4 (Stage B2-C) carcinoma of the prostate. Treatment with ZOLADEX and flutamide should start 8 weeks prior to initiating radiation therapy and continue during radiation therapy [see Dosage and Administration (2.1) and Clinical Studies (14.1)].

1.2 Prostatic Carcinoma

ZOLADEX is indicated in the palliative treatment of advanced carcinoma of the prostate [see Dosage and Administration (2.2) and Clinical Studies (14.2)].

1.3 Endometriosis

ZOLADEX is indicated for the management of endometriosis, including pain relief and reduction of endometriotic lesions for the duration of therapy. Experience with ZOLADEX for the management of endometriosis has been limited to women 18 years of age and older treated for 6 months [see Dosage and Administration (2.3) and Clinical Studies (14.3)].

1.4 Endometrial Thinning

ZOLADEX is indicated for use as an endometrial-thinning agent prior to endometrial ablation for dysfunctional uterine bleeding [see Dosage and Administration (2.4) and Clinical Studies (14.4)].

1.5 Advanced Breast Cancer

ZOLADEX is indicated for use in the palliative treatment of advanced breast cancer in pre- and perimenopausal women.

The estrogen and progesterone receptor values may help to predict whether ZOLADEX therapy is likely to be beneficial [see Dosage and Administration (2.5), Clinical Pharmacology (12.1), and Clinical Studies (14.5)].

The automatic safety feature of the syringe aids in the prevention of needlestick injury.

2 DOSAGE AND ADMINISTRATION

ZOLADEX, at a dose of 3.6 mg, should be administered subcutaneously every 28 days into the anterior abdominal wall below the navel line using an aseptic technique under the supervision of a physician [see Dosage and Administration (2.7)].

While a delay of a few days is permissible, every effort should be made to adhere to the 28-day schedule.

2.1 Stage B2-C Prostatic Carcinoma

When ZOLADEX is given in combination with radiotherapy and flutamide for patients with Stage T2b-T4 (Stage B2-C) prostatic carcinoma, treatment should be started 8 weeks prior to initiating radiotherapy and should continue during radiation therapy. A treatment regimen using a ZOLADEX 3.6 mg depot 8 weeks before radiotherapy, followed in 28 days by the ZOLADEX 10.8 mg depot, can be administered. Alternatively, four injections of 3.6 mg depot can be administered at 28-day intervals, two depots preceding and two during radiotherapy.

2.2 Prostatic Carcinoma

For the management of advanced prostate cancer, ZOLADEX is intended for long-term administration unless clinically inappropriate.

2.3 Endometriosis

For the management of endometriosis, the recommended duration of administration is 6 months.

Currently, there are no clinical data on the effect of treatment of benign gynecological conditions with ZOLADEX for periods in excess of 6 months.

Retreatment cannot be recommended for the management of endometriosis since safety data for retreatment are not available. If the symptoms of endometriosis recur after a course of therapy, and further treatment with ZOLADEX is contemplated, consideration should be given to monitoring bone mineral density. Clinical studies suggest the addition of Hormone Replacement Therapy (estrogens and/or progestins) to ZOLADEX is effective in reducing the bone mineral loss which occurs with ZOLADEX alone without compromising the efficacy of ZOLADEX in relieving the symptoms of endometriosis. The addition of Hormone Replacement Therapy may also reduce the occurrence of vasomotor symptoms and vaginal dryness associated with hypoestrogenism. The optimal drugs, dose and duration of treatment has not been established.

2.4 Endometrial Thinning

For use as an endometrial-thinning agent prior to endometrial ablation, the dosing recommendation is one or two depots (with each depot given four weeks apart). When one depot is administered, surgery should be performed at four weeks. When two depots are administered, surgery should be performed within two to four weeks following administration of the second depot.

2.5 Breast Cancer

For the management of advanced breast cancer, ZOLADEX is intended for long-term administration unless clinically inappropriate.

2.6 Renal or Hepatic Impairment

No dosage adjustment is necessary for patients with renal or hepatic impairment.

2.7 Administration Technique

The proper method of administration of ZOLADEX is described in the instructions that follow.

1. Put the patient in a comfortable position with the upper part of the body slightly raised. Prepare an area of the anterior abdominal wall below the navel line with an alcohol swab.
  NOTE: Caution should be taken while injecting ZOLADEX into the anterior abdominal wall due to the proximity of underlying inferior epigastric artery and its branches.
2. Examine the foil pouch and syringe for damage. Remove the syringe from the opened foil pouch and hold the syringe at a slight angle to the light. Check that at least part of the ZOLADEX implant is visible.
  NOTE: do not remove the syringe by the plunger.
3. Grasp the red plastic safety tab and pull away from the syringe, and discard. Remove needle cover. Unlike liquid injections, there is no need to remove air bubbles as attempts to do so may displace the ZOLADEX implant.
4. Holding the syringe around the protective sleeve, using an aseptic technique, pinch the skin of the patient's anterior abdominal wall below the navel line. With the bevel of the needle facing up, insert the needle at a 30 to 45 degree angle to the skin in one continuous deliberate motion until the protective sleeve touches the patient's skin.
  NOTE: The ZOLADEX syringe cannot be used for aspiration. If the hypodermic needle penetrates a large vessel, blood will be seen instantly in the syringe chamber. If a vessel is penetrated, withdraw the needle and inject with a new syringe elsewhere. Monitor patients for signs or symptoms of abdominal hemorrhage. Use extra care when administering ZOLADEX to patients with a low BMI and/or to patients receiving full dose anticoagulation [see Warnings and Precautions (5.10)].
5. Do not penetrate into muscle or peritoneum.
6. To administer the ZOLADEX implant and to activate the protective sleeve, grasp the barrel at the finger grip and depress the plunger until you cannot depress it any further. If the plunger is not depressed fully, the protective sleeve will NOT activate. When the protective sleeve ‘clicks’, the protective sleeve will automatically begin to slide to cover the needle.
  NOTE: The needle does not retract.
7. Withdraw the needle and allow protective sleeve to slide and cover needle. Dispose of the syringe in an approved sharps collector.

NOTE: In the unlikely event of the need to surgically remove ZOLADEX, it may be localized by ultrasound.

3 DOSAGE FORMS AND STRENGTHS

ZOLADEX is supplied as a sterile and totally biodegradable D,L-lactic and glycolic acids copolymer impregnated with 3.8 mg goserelin acetate, equivalent to 3.6 mg of goserelin, in a disposable syringe device fitted with a 16-gauge x 36 +/- 0.5 mm siliconized hypodermic needle with protective needle sleeve [SafeSystem® Syringe] (NDC 70720-950-36).

4 CONTRAINDICATIONS

4.1 Hypersensitivity

Anaphylactic reactions to ZOLADEX have been reported in the medical literature. ZOLADEX is contraindicated in those patients who have a known hypersensitivity to GnRH, GnRH agonist analogues or any of the components in ZOLADEX [see Warnings and Precautions (5.6)].

4.2 Pregnancy

ZOLADEX is contraindicated during pregnancy unless ZOLADEX is being used for palliative treatment of advanced breast cancer. ZOLADEX can cause fetal harm when administered to a pregnant woman. If this drug is used during pregnancy, the patient should be apprised of the potential hazard to the fetus. There is an increased risk for pregnancy loss due to expected hormone changes that occur with ZOLADEX treatment [see Use in Specific Populations (8.1)].

5 WARNINGS AND PRECAUTIONS

5.1 Women of Childbearing Potential and Pregnancy

Before starting treatment with ZOLADEX, pregnancy must be excluded for women using ZOLADEX for benign gynecological conditions. Women of childbearing potential should be advised to avoid becoming pregnant.

Effective nonhormonal contraception must be used by all premenopausal women during ZOLADEX therapy and for 12 weeks following discontinuation of therapy. When used every 28 days, ZOLADEX usually inhibits ovulation and stops menstruation; however, pregnancy prevention is not ensured. Effects on reproductive function are expected to occur with chronic administration as a result of the anti-gonadotrophic properties of the drug.

Based on mechanism of action in humans and findings of increased pregnancy loss in animal studies, ZOLADEX can cause fetal harm when administered to a pregnant woman. If this drug is used during pregnancy for the palliative treatment of breast cancer, then the patient should be apprised of the potential hazard to the fetus [see Use in Specific Populations (8.1)].

5.2 Tumor Flare Phenomenon

Initially, ZOLADEX, like other GnRH agonists, causes transient increases in serum levels of testosterone in men with prostate cancer, and estrogen in women with breast cancer. Transient worsening of symptoms, or the occurrence of additional signs and symptoms of prostate or breast cancer, may occasionally develop during the first few weeks of ZOLADEX treatment. A small number of patients may experience a temporary increase in bone pain, which can be managed symptomatically.

As with other GnRH agonists, isolated cases of ureteral obstruction and spinal cord compression have been observed in patients with prostate cancer. If spinal cord compression or renal impairment secondary to ureteral obstruction develops, standard treatment of these complications should be instituted. For extreme cases in prostate cancer patients, an immediate orchiectomy should be considered.

5.3 Hyperglycemia and Diabetes

Hyperglycemia and an increased risk of developing diabetes have been reported in men receiving GnRH agonists. Hyperglycemia may represent development of diabetes mellitus or worsening of glycemic control in patients with diabetes. Monitor blood glucose and/or glycosylated hemoglobin (HbA1c) periodically in patients receiving a GnRH agonist and manage with current practice for treatment of hyperglycemia or diabetes [see Patient Counseling Information (17.2)].

5.4 Cardiovascular Diseases

Increased risk of developing myocardial infarction, sudden cardiac death and stroke has been reported in association with use of GnRH agonists in men. The risk appears low based on the reported odds ratios, and should be evaluated carefully along with cardiovascular risk factors when determining a treatment for patients with prostate cancer. Patients receiving a GnRH agonist should be monitored for symptoms and signs suggestive of development of cardiovascular disease and be managed according to current clinical practice [see Patient Counseling Information (17.2)].

5.5 Hypercalcemia

As with other GnRH agonists or hormonal therapies (antiestrogens, estrogens, etc.), hypercalcemia has been reported in some prostate and breast cancer patients with bone metastases after starting treatment with ZOLADEX. If hypercalcemia does occur, appropriate treatment measures should be initiated.

5.6 Hypersensitivity

Hypersensitivity, antibody formation and acute anaphylactic reactions have been reported with GnRH agonist analogues [see Contraindications (4.1)].

Of 115 women worldwide treated with ZOLADEX and tested for development of binding to goserelin following treatment with ZOLADEX, one patient showed low-titer binding to goserelin. On further testing of this patient's plasma obtained following treatment, her goserelin binding component was found not to be precipitated with rabbit antihuman immunoglobulin polyvalent sera. These findings suggest the possibility of antibody formation.

5.7 Severe Cutaneous Adverse Reactions

ZOLADEX can cause severe cutaneous adverse reactions (SCARs), including Stevens-Johnson syndrome/toxic epidermal necrolysis (SJS/TEN), drug reaction with eosinophilia and systemic symptoms (DRESS), and acute generalized exanthematous pustulosis (AGEP). SCARs, including SJS/TEN, DRESS, and AGEP, occurred in patients receiving ZOLADEX or other GnRH agonists; including cases with visceral involvement and/or requiring skin grafts [see Adverse Reactions (6.10) and Patient Counseling Information (17.1)].

Monitor patients for the development of SCARs.

If a SCAR is suspected, interrupt ZOLADEX until the etiology of the reaction has been determined. Consultation with a dermatologist is recommended. If a SCAR is confirmed, or for other grade 4 skin reactions, permanently discontinue ZOLADEX.

5.8 Cervical Resistance

The pharmacologic action of ZOLADEX on the uterus and cervix may cause an increase in cervical resistance. Therefore, care should be taken when dilating the cervix for endometrial ablation.

5.9 Effect on QT/QTc Interval

Androgen deprivation therapy may prolong the QT/QTc interval. Providers should consider whether the benefits of androgen deprivation therapy outweigh the potential risks in patients with congenital long QT syndrome, congestive heart failure, frequent electrolyte abnormalities, and in patients taking drugs known to prolong the QT interval. Electrolyte abnormalities should be corrected. Consider periodic monitoring of electrocardiograms and electrolytes.

5.10 Injection Site Injury

Injection site injury and vascular injury including pain, hematoma, hemorrhage and hemorrhagic shock, requiring blood transfusions and surgical intervention, have been reported with ZOLADEX. Extra care should be taken when administering ZOLADEX to patients with a low BMI and/or to patients receiving full dose anticoagulation [see Dosage and Administration (2.7) and Patient Counseling Information (17.2 and 17.3)].

5.11 Clinical Depression

Depression may occur or worsen in women during treatment with GnRH agonists including ZOLADEX 3.6 mg [see Adverse Reactions (6.4, 6.5, 6.10)]. Carefully observe women for depression, especially those with a history of depression and consider whether the risks of continuing ZOLADEX 3.6 mg outweigh the benefits. Women with new or worsening depression should be referred to a mental health professional, as appropriate.

6 ADVERSE REACTIONS

6.1 Stage B2-C Prostatic Carcinoma

Treatment with ZOLADEX and flutamide did not add substantially to the toxicity of radiation treatment alone. The following adverse experiences were reported during a multicenter clinical trial comparing ZOLADEX + flutamide + radiation versus radiation alone. The most frequently reported (greater than 5%) adverse experiences are listed below:

Table 1 ADVERSE EVENTS DURING ACUTE RADIATION THERAPY (within first 90 days of radiation therapy)
 | (n=231) flutamide + ZOLADEX + Radiation % All | (n=235) Radiation Only % All
Rectum/Large Bowel | 80 | 76
Bladder | 58 | 60
Skin | 37 | 37

Table 2 ADVERSE EVENTS DURING LATE RADIATION PHASE (after 90 days of radiation therapy)
 | (n=231) flutamide + ZOLADEX + Radiation % All | (n=235) Radiation Only % All
Diarrhea | 36 | 40
Cystitis | 16 | 16
Rectal Bleeding | 14 | 20
Proctitis | 8 | 8
Hematuria | 7 | 12

Additional adverse event data was collected for the combination therapy with radiation group over both the hormonal treatment and hormonal treatment plus radiation phases of the study. Adverse experiences occurring in more than 5% of patients in this group, over both parts of the study, were hot flashes (46%), diarrhea (40%), nausea (9%), and skin rash (8%).

6.2 Prostatic Carcinoma

ZOLADEX has been found to be generally well tolerated in clinical trials. Adverse reactions reported in these trials were rarely severe enough to result in the patients’ withdrawal from ZOLADEX treatment. As seen with other hormonal therapies, the most commonly observed adverse events during ZOLADEX therapy were due to the expected physiological effects from decreased testosterone levels. These included hot flashes, sexual dysfunction and decreased erections.

Tumor Flare Phenomenon: Initially, ZOLADEX, like other GnRH agonists, causes transient increases in serum levels of testosterone. A small percentage of patients experienced a temporary worsening of signs and symptoms, usually manifested by an increase in cancer-related pain which was managed symptomatically. Isolated cases of exacerbation of disease symptoms, either ureteral obstruction or spinal cord compression, occurred at similar rates in controlled clinical trials with both ZOLADEX and orchiectomy. The relationship of these events to therapy is uncertain [see Warnings and Precautions (5.2)].

In the controlled clinical trials of ZOLADEX versus orchiectomy, the following events were reported as adverse reactions in greater than 5% of the patients.

Table 3 TREATMENT RECEIVED
 | ZOLADEX (n=242) | ORCHIECTOMY (n=254)
ADVERSE EVENT | % | %
Hot Flashes | 62 | 53
Sexual Dysfunction | 21 | 15
Decreased Erections | 18 | 16
Lower Urinary Tract Symptoms | 13 | 8
Lethargy | 8 | 4
Pain (worsened in the first 30 days) | 8 | 3
Edema | 7 | 8
Upper Respiratory Infection | 7 | 2
Rash | 6 | 1
Sweating | 6 | 4
Anorexia | 5 | 2
Chronic Obstructive Pulmonary Disease | 5 | 3
Congestive Heart Failure | 5 | 1
Dizziness | 5 | 4
Insomnia | 5 | 1
Nausea | 5 | 2
Complications of Surgery | 0 | 18^1
1. Complications related to surgery were reported in 18% of the orchiectomy patients, while only 3% of ZOLADEX patients reported adverse reactions at the injection site. The surgical complications included scrotal infection (5.9%), groin pain (4.7%), wound seepage (3.1%), scrotal hematoma (2.8%), incisional discomfort (1.6%) and skin necrosis (1.2%).

The following additional adverse reactions were reported in greater than 1% but less than 5% of the patients treated with ZOLADEX: CARDIOVASCULAR – arrhythmia, cerebrovascular accident, hypertension, myocardial infarction, peripheral vascular disorder, chest pain; CENTRAL NERVOUS SYSTEM – anxiety, depression, headache; GASTROINTESTINAL – constipation, diarrhea, ulcer, vomiting; HEMATOLOGIC – anemia; METABOLIC/NUTRITIONAL – gout, hyperglycemia, weight increase; MISCELLANEOUS – chills, fever; UROGENITAL – renal insufficiency, urinary obstruction, urinary tract infection, breast swelling and tenderness.

6.3 Females

As would be expected with a drug that results in hypoestrogenism, the most frequently reported adverse reactions were those related to this effect.

6.4 Endometriosis

In controlled clinical trials comparing ZOLADEX every 28 days and danazol daily for the treatment of endometriosis, the following events were reported at a frequency of 5% or greater.

Table 4 TREATMENT RECEIVED
 | ZOLADEX (n=411) | DANAZOL (n=207)
ADVERSE EVENT | % | %
Hot Flushes | 96 | 67
Vaginitis | 75 | 43
Headache | 75 | 63
Emotional Lability | 60 | 56
Libido Decreased | 61 | 44
Sweating | 45 | 30
Depression | 54 | 48
Acne | 42 | 55
Breast Atrophy | 33 | 42
Seborrhea | 26 | 52
Peripheral Edema | 21 | 34
Breast Enlargement | 18 | 15
Pelvic Symptoms | 18 | 23
Pain | 17 | 16
Dyspareunia | 14 | 5
Libido Increased | 12 | 19
Infection | 13 | 11
Asthenia | 11 | 13
Nausea | 8 | 14
Hirsutism | 7 | 15
Insomnia | 11 | 4
Breast Pain | 7 | 4
Abdominal Pain | 7 | 7
Back Pain | 7 | 13
Flu Syndrome | 5 | 5
Dizziness | 6 | 4
Application Site Reaction | 6 | -
Voice Alterations | 3 | 8
Pharyngitis | 5 | 2
Hair Disorders | 4 | 11
Myalgia | 3 | 11
Nervousness | 3 | 5
Weight Gain | 3 | 23
Leg Cramps | 2 | 6
Increased Appetite | 2 | 5
Pruritus | 2 | 6
Hypertonia | 1 | 10

The following adverse events not already listed above were reported at a frequency of 1% or greater, regardless of causality, in ZOLADEX-treated women from all clinical trials: WHOLE BODY – allergic reaction, chest pain, fever, malaise; CARDIOVASCULAR – hemorrhage, hypertension, migraine, palpitations, tachycardia; DIGESTIVE – anorexia, constipation, diarrhea, dry mouth, dyspepsia, flatulence; HEMATOLOGIC – ecchymosis; METABOLIC AND NUTRITIONAL – edema; MUSCULOSKELETAL – arthralgia, joint disorder; CNS – anxiety, paresthesia, somnolence, thinking abnormal; RESPIRATORY – bronchitis, cough increased, epistaxis, rhinitis, sinusitis; SKIN – alopecia, dry skin, rash, skin discoloration; SPECIAL SENSES – amblyopia, dry eyes; UROGENITAL – dysmenorrhea, urinary frequency, urinary tract infection, vaginal hemorrhage.

6.5 Endometrial Thinning

The following adverse events were reported at a frequency of 5% or greater in premenopausal women presenting with dysfunctional uterine bleeding in Trial 0022 for endometrial thinning. These results indicate that headache, hot flushes and sweating were more common in the ZOLADEX group than in the placebo group.

Table 5 ADVERSE EVENTS REPORTED AT A FREQUENCY OF 5% OR GREATER IN ZOLADEX AND PLACEBO TREATMENT GROUPS OF TRIAL 0022
 | ZOLADEX 3.6 mg (n=180) | Placebo (n=177)
ADVERSE EVENT | % | %
Whole Body
Headache | 32 | 22
Abdominal Pain | 11 | 10
Pelvic Pain | 9 | 6
Back Pain | 4 | 7
Cardiovascular
Vasodilatation | 57 | 18
Migraine | 7 | 4
Hypertension | 6 | 2
Digestive
Nausea | 5 | 6
Nervous
Nervousness | 5 | 3
Depression | 3 | 7
Respiratory
Pharyngitis | 6 | 9
Sinusitis | 3 | 6
Skin and appendages
Sweating | 16 | 5
Urogenital
Dysmenorrhea | 7 | 9
Uterine Hemorrhage | 6 | 4
Vulvovaginitis | 5 | 1
Menorrhagia | 4 | 5
Vaginitis | 1 | 6

6.6 Breast Cancer

The adverse event profile for women with advanced breast cancer treated with ZOLADEX is consistent with the profile described above for women treated with ZOLADEX for endometriosis. In a controlled clinical trial (SWOG–8692) comparing ZOLADEX with oophorectomy in premenopausal and perimenopausal women with advanced breast cancer, the following events were reported at a frequency of 5% or greater in either treatment group regardless of causality.

Table 6 TREATMENT RECEIVED
 | ZOLADEX (n=57) | OOPHORECTOMY (n=55)
ADVERSE EVENT | % of Pts. | % of Pts.
Hot Flashes | 70 | 47
Tumor Flare | 23 | 4
Nausea | 11 | 7
Edema | 5 | 0
Malaise/Fatigue/Lethargy | 5 | 2
Vomiting | 4 | 7

In the Phase II clinical trial program in 333 pre- and perimenopausal women with advanced breast cancer, hot flashes were reported in 75.9% of patients and decreased libido was noted in 47.7% of patients. These two adverse events reflect the pharmacological actions of ZOLADEX.

Injection site reactions were reported in less than 1% of patients.

6.7 Hormone Replacement Therapy

Clinical studies suggest the addition of Hormone Replacement Therapy (estrogens and/or progestins) to ZOLADEX may decrease the occurrence of vasomotor symptoms and vaginal dryness associated with hypoestrogenism without compromising the efficacy of ZOLADEX in relieving pelvic symptoms. The optimal drugs, dose and duration of treatment has not been established.

6.8 Changes in Bone Mineral Density

After 6 months of ZOLADEX treatment, 109 female patients treated with ZOLADEX showed an average 4.3% decrease of vertebral trabecular bone mineral density (BMD) as compared to pretreatment values. BMD was measured by dual-photon absorptiometry or dual energy x-ray absorptiometry. Sixty-six of these patients were assessed for BMD loss 6 months after the completion (posttherapy) of the 6-month therapy period. Data from these patients showed an average 2.4% BMD loss compared to pretreatment values.

Twenty-eight of the 109 patients were assessed for BMD at 12 months posttherapy. Data from these patients showed an average decrease of 2.5% in BMD compared to pretreatment values. These data suggest a possibility of partial reversibility. Clinical studies suggest the addition of Hormone Replacement Therapy (estrogens and/or progestins) to ZOLADEX is effective in reducing the bone mineral loss which occurs with ZOLADEX alone without compromising the efficacy of ZOLADEX in relieving the symptoms of endometriosis. The optimal drugs, dose and duration of treatment has not been established [see Patient Counseling Information (17.3)].

6.9 Changes in Laboratory Values During Treatment

Plasma Enzymes: Elevation of liver enzymes (AST, ALT) have been reported in female patients exposed to ZOLADEX (representing less than 1% of all patients).

Lipids: In a controlled trial, ZOLADEX therapy resulted in a minor, but statistically significant effect on serum lipids. In patients treated for endometriosis at 6 months following initiation of therapy, danazol treatment resulted in a mean increase in LDL cholesterol of 33.3 mg/dL and a decrease in HDL cholesterol of 21.3 mg/dL compared to increases of 21.3 and 2.7 mg/dL in LDL cholesterol and HDL cholesterol, respectively, for ZOLADEX-treated patients. Triglycerides increased by 8.0 mg/dL in ZOLADEX-treated patients compared to a decrease of 8.9 mg/dL in danazol-treated patients.

In patients treated for endometriosis, ZOLADEX increased total cholesterol and LDL cholesterol during 6 months of treatment. However, ZOLADEX therapy resulted in HDL cholesterol levels which were significantly higher relative to danazol therapy. At the end of 6 months of treatment, HDL cholesterol fractions (HDL2 and HDL3) were decreased by 13.5 and 7.7 mg/dL, respectively, for danazol-treated patients compared to treatment increases of 1.9 and 0.8 mg/dL, respectively, for ZOLADEX-treated patients.

6.10 Postmarketing Experience

The following adverse reactions have been identified during post-approval use of ZOLADEX. Because these reactions are reported voluntarily from a population of uncertain size, it is not always possible to reliably estimate their frequency or establish a causal relationship to drug exposure.

Bone Mineral Density: Osteoporosis, decreased bone mineral density and bone fracture in men [see Patient Counseling Information (17.2) and (17.3)].

Cardiovascular: Deep vein thrombosis, pulmonary embolism, myocardial infarction, stroke, and transient ischemic attack have been observed in women treated with GnRH agonists. Although a temporal relationship was reported in some cases, most cases were confounded by risk factors or concomitant medication use. It is unknown if there is a causal association between the use of GnRH analogs and these events.

Ovarian Cyst: Ovarian cyst formation and, in combination with gonadotropins, ovarian hyperstimulation syndrome (OHSS).

Changes in Blood Pressure: Hypotension and hypertension have been reported. These changes are usually transient, resolving either during continued therapy or after cessation of therapy.

Pituitary Apoplexy and Tumors: Pituitary apoplexy (a clinical syndrome secondary to infarction of the pituitary gland) and pituitary adenoma have been diagnosed. Most of the pituitary apoplexy cases occurred within 2 weeks of the first dose, and some occurred within the first hour. In these cases, pituitary apoplexy has presented as sudden headache, vomiting, visual changes, ophthalmoplegia, altered mental status, and sometimes cardiovascular collapse. Immediate medical attention has been required. Pituitary tumors have been reported.

Acne: Usually within one month of starting treatment.

Skin reactions: SJS/TEN, DRESS, AGEP, dermatitis exfoliative, bullous dermatitis, and erythema multiforme.

Other Adverse Reactions: Psychotic disorders, convulsions and mood swings, including depression; suicidal ideation and attempt in women.

7 DRUG INTERACTIONS

No formal drug-drug interaction studies have been performed. No confirmed interactions have been reported between ZOLADEX and other drugs.

7.1 Drug/Laboratory Test Interactions

Administration of ZOLADEX in therapeutic doses results in suppression of the pituitary-gonadal system. Because of this suppression, diagnostic tests of pituitary-gonadotropic and gonadal functions conducted during treatment and until the resumption of menses may show results which are misleading. Normal function is usually restored within 12 weeks after treatment is discontinued.

8 USE IN SPECIFIC POPULATIONS

8.1 Pregnancy

ZOLADEX is contraindicated during pregnancy unless ZOLADEX is being used for palliative treatment of advanced breast cancer. There are no adequate and well-controlled studies in pregnant women using ZOLADEX. Based on mechanism of action in humans and findings of increased pregnancy loss in animal studies, ZOLADEX can cause fetal harm when administered to a pregnant woman. If this drug is used during pregnancy, the patient should be apprised of the potential hazard to the fetus. There is an increased risk for pregnancy loss due to expected hormone changes that occur with ZOLADEX treatment.

ZOLADEX crosses the placenta in rats and rabbits following subcutaneous administration. Administration of goserelin to pregnant rats and rabbits during organogenesis resulted in increased preimplantation loss and increased resorptions. When pregnant rats received goserelin throughout gestation and lactation, there was a dose-related increase in umbilical hernia in offspring. In additional reproduction studies in rats, goserelin decreased fetus and pup survival. Human dose/exposure multiples could not be calculated from available animal data.

Actual animal doses: rat (≥ 2 mcg/kg/day for pregnancy loss; > 10 mcg/kg/day for umbilical hernia in offspring); rabbits (> 20 mcg/kg/day).

8.3 Nursing Mothers

It is not known if goserelin is excreted in human milk. Goserelin is excreted in the milk of lactating rats. Because many drugs are excreted in human milk and because of the potential for serious adverse reactions in nursing infants from ZOLADEX, a decision should be made to either discontinue nursing or discontinue the drug, taking into account the importance of the drug to the mother.

8.4 Pediatric Use

Safety and effectiveness in pediatric patients have not been established.

8.5 Geriatric Use

There is no need for any dosage adjustment when administering ZOLADEX to male geriatric patients. ZOLADEX has not been studied in women over 65 years.

8.6 Renal Insufficiency

In clinical trials with the solution formulation of goserelin, male patients with impaired renal function (creatinine clearance < 20 mL/min) had a total body clearance and serum elimination half-life of 31.5 mL/min and 12.1 hours, respectively, compared to 133 mL/min and 4.2 hours for subjects with normal renal function (creatinine clearance > 70 mL/min). In females, the effects of reduced goserelin clearance due to impaired renal function on drug efficacy and toxicity are unknown. Pharmacokinetic studies in patients with renal impairment do not indicate a need for dose adjustment with the use of the depot formulation.

8.7 Hepatic Insufficiency

The total body clearances and serum elimination half-lives were similar between normal subjects and patients with moderate hepatic impairment (alanine transaminase < 3xULN and asparate aminotransferase < 3xULN) when treated with a 250 mcg subcutaneous formulation of goserelin. This pharmacokinetic study indicates that no dose adjustment is needed in patients with moderately impaired liver function.

There is no pharmacokinetic data with goserelin in patients with severe hepatic insufficiency.

10 OVERDOSAGE

The pharmacologic properties of ZOLADEX and its mode of administration make accidental or intentional overdosage unlikely. There is no experience of overdosage from clinical trials. Animal studies indicate that no increased pharmacologic effect occurred at higher doses or more frequent administration. Subcutaneous doses of the drug as high as 1 mg/kg/day in rats and dogs did not produce any nonendocrine related sequelae; this dose is up to 250 times the estimated human daily dose based on the body surface area. If overdosage occurs, it should be managed symptomatically.

11 DESCRIPTION

ZOLADEX (goserelin implant) is a GnRH agonist. Goserelin acetate is chemically described as an acetate salt of [D-Ser(But)^6,Azgly^10]. Its chemical structure is pyro-Glu-His-Trp-Ser-Tyr-D-Ser(But)-Leu-Arg-Pro-Azgly-NH2 acetate [C59H84N18O14·(C2H4O2)x where x = 1 to 2.4].

Goserelin acetate is an off-white powder with a molecular weight of 1269 Daltons (free base). It is freely soluble in glacial acetic acid. It is soluble in water, 0.1M hydrochloric acid, 0.1M sodium hydroxide, dimethylformamide and dimethyl sulfoxide. Goserelin acetate is practically insoluble in acetone, chloroform and ether.

ZOLADEX is supplied as a sterile, biodegradable product containing 3.8 mg goserelin acetate, equivalent to 3.6 mg of goserelin. ZOLADEX is designed for subcutaneous injection with continuous release over a 28-day period. Goserelin acetate, containing up to 12% goserelin-related substances, is dispersed in a matrix of D,L-lactic and glycolic acids copolymer (to a total implant weight of 18.0 mg, containing less than 2.5% total acetic acid) and presented as a sterile, white to cream colored 1-mm diameter cylinder, preloaded in a special single use syringe with a 16-gauge x 36 +/- 0.5 mm siliconized needle with protective needle sleeve (SafeSystem® Syringe) in a sealed, light- and moisture-proof, aluminum foil laminate pouch containing a desiccant capsule. Studies of the D,L-lactic and glycolic acids copolymer have indicated that it is completely biodegradable and has no demonstrable antigenic potential.

12 CLINICAL PHARMACOLOGY

12.1 Mechanism of Action

ZOLADEX is a synthetic decapeptide analogue of GnRH. ZOLADEX acts as an inhibitor of pituitary gonadotropin secretion when administered in the biodegradable formulation. In animal and in vitro studies, administration of goserelin resulted in the regression or inhibition of growth of the hormonally sensitive dimethylbenzanthracene (DMBA)-induced rat mammary tumor and Dunning R3327 prostate tumor.

12.2 Pharmacodynamics

Following initial administration in males, ZOLADEX causes an initial increase in serum luteinizing hormone (LH) and follicle stimulating hormone (FSH) levels with subsequent increases in serum levels of testosterone. Chronic administration of ZOLADEX leads to sustained suppression of pituitary gonadotropins, and serum levels of testosterone consequently fall into the range normally seen in surgically castrated men approximately 2-4 weeks after initiation of therapy. This leads to accessory sex organ regression. In clinical trials with follow-up of more than 2 years, suppression of serum testosterone to castrate levels has been maintained for the duration of therapy.

In females, a similar down-regulation of the pituitary gland by chronic exposure to ZOLADEX leads to suppression of gonadotropin secretion, a decrease in serum estradiol to levels consistent with the postmenopausal state, and would be expected to lead to a reduction of ovarian size and function, reduction in the size of the uterus and mammary gland, as well as a regression of sex hormone-responsive tumors, if present. Serum estradiol is suppressed to levels similar to those observed in postmenopausal women within 3 weeks following initial administration; however, after suppression was attained, isolated elevations of estradiol were seen in 10% of the patients enrolled in clinical trials. Serum LH and FSH are suppressed to follicular phase levels within four weeks after initial administration of drug and are usually maintained at that range with continued use of ZOLADEX. In 5% or less of women treated with ZOLADEX, FSH and LH levels may not be suppressed to follicular phase levels on day 28 post treatment with use of a single 3.6 mg depot injection. In certain individuals, suppression of any of these hormones to such levels may not be achieved with ZOLADEX. Estradiol, LH and FSH levels return to pretreatment values within 12 weeks following the last implant administration in all but rare cases.

12.3 Pharmacokinetics

The pharmacokinetics of ZOLADEX have been determined in both male and female healthy volunteers and patients. In these studies, ZOLADEX was administered as a single 250 mcg (aqueous solution) dose and as a single or multiple 3.6 mg depot dose by subcutaneous route.

Absorption

The absorption of radiolabeled drug was rapid, and the peak blood radioactivity levels occurred between 0.5 and 1.0 hour after dosing. The mean (± standard deviation) pharmacokinetic parameter estimates of ZOLADEX after administration of 3.6 mg depot for 2 months in males and females are presented in the following table.

Table 7 PHARMACOKINETIC PARAMETER ESTIMATES
Parameter (units) | Males n=7 | Females n=9
Peak Plasma Concentration (ng/mL) | 2.84 ± 1.81 | 1.46 ± 0.82
Time to Peak Concentration (days) | 12-15 | 8-22
Area Under the Curve (0-28 days) (ng.d/mL) | 27.8 ± 15.3 | 18.5 ± 10.3
Systemic Clearance (mL/min) | 110.5 ± 47.5 | 163.9 ± 71.0

Goserelin is released from the depot at a much slower rate initially for the first 8 days, and then there is more rapid and continuous release for the remainder of the 28-day dosing period. Despite the change in the releasing rate of goserelin, administration of ZOLADEX every 28 days resulted in testosterone levels that were suppressed to and maintained in the range normally seen in surgically castrated men.

When ZOLADEX 3.6 mg depot was used for treating male and female patients with normal renal and hepatic function, there was no significant evidence of drug accumulation. However, in clinical trials the minimum serum levels of a few patients were increased. These levels can be attributed to interpatient variation.

Distribution

The apparent volumes of distribution determined after subcutaneous administration of 250 mcg aqueous solution of goserelin were 44.1 and 20.3 liters for males and females, respectively. The plasma protein binding of goserelin obtained from one sample was found to be 27.3%.

Metabolism

Metabolism of goserelin, by hydrolysis of the C-terminal amino acids, is the major clearance mechanism. The major circulating component in serum appeared to be 1–7 fragment, and the major component presented in urine of one healthy male volunteer was 5-10 fragment. The metabolism of goserelin in humans yields a similar but narrow profile of metabolites to that found in other species. All metabolites found in humans have also been found in toxicology species.

Excretion

Clearance of goserelin following subcutaneous administration of the solution formulation of goserelin is very rapid and occurs via a combination of hepatic metabolism and urinary excretion. More than 90% of a subcutaneous radiolabeled solution formulation dose of goserelin is excreted in urine. Approximately 20% of the dose in urine is accounted for by unchanged goserelin. The total body clearance of goserelin (administered subcutaneously as a 3.6 mg depot) was significantly (p<0.05) greater (163.9 versus 110.5 L/min) in females compared to males.

13 NONCLINICAL TOXICOLOGY

13.1 Carcinogenesis, Mutagenesis, Impairment of Fertility

Subcutaneous implantation of goserelin in male and female rats once every 4 weeks for 1 year and recovery for 23 weeks at doses of about 80 and 150 mcg/kg (males) and 50 and 100 mcg/kg (females) daily resulted in an increased incidence of pituitary adenomas. An increased incidence of pituitary adenomas was also observed following subcutaneous implant of goserelin in rats at similar dose levels for a period of 72 weeks in males and 101 weeks in females. The relevance of the rat pituitary adenomas to humans has not been established. Subcutaneous implants of goserelin every 3 weeks for 2 years delivered to mice at doses of up to 2400 mcg/kg/day resulted in an increased incidence of histiocytic sarcoma of the vertebral column and femur. Human dose/exposure multiples could not be calculated from available animal data.

Mutagenicity tests using bacterial and mammalian systems for point mutations and cytogenetic effects have provided no evidence for mutagenic potential.

Administration of goserelin led to changes that were consistent with gonadal suppression in both male and female rats as a result of its endocrine action. In male rats administered 500-1000 mcg/kg/day, a decrease in weight and atrophic histological changes were observed in the testes, epididymis, seminal vesicle and prostate gland with complete suppression of spermatogenesis. In female rats administered 50-1000 mcg/kg/day, suppression of ovarian function led to decreased size and weight of ovaries and secondary sex organs; follicular development was arrested at the antral stage and the corpora lutea were reduced in size and number. Except for the testes, almost complete histologic reversal of these effects in males and females was observed several weeks after dosing was stopped; however, fertility and general reproductive performance were reduced in those that became pregnant after goserelin was discontinued. Fertile matings occurred within 2 weeks after cessation of dosing, even though total recovery of reproductive function may not have occurred before mating took place; and, the ovulation rate, the corresponding implantation rate, and number of live fetuses were reduced.

Based on histological examination, drug effects on reproductive organs were reversible in male and female dogs administered 107-214 mcg/kg/day goserelin when drug treatment was stopped after continuous administration for 1 year. Human dose/exposure multiples could not be calculated from available animal data.

14 CLINICAL STUDIES

14.1 Stage B2-C Prostatic Carcinoma

The effects of hormonal treatment combined with radiation were studied in 466 patients (231 ZOLADEX + flutamide + radiation, 235 radiation alone) with bulky primary tumors confined to the prostate (stage B2) or extending beyond the capsule (stage C), with or without pelvic node involvement.

In this multicentered, controlled trial, administration of ZOLADEX (3.6 mg depot) and flutamide capsules (250 mg t.i.d.) prior to and during radiation was associated with a significantly lower rate of local failure compared to radiation alone (16% vs 33% at 4 years, P<0.001). The combination therapy also resulted in a trend toward reduction in the incidence of distant metastases (27% vs 36% at 4 years, P=0.058). Median disease-free survival was significantly increased in patients who received complete hormonal therapy combined with radiation as compared to those patients who received radiation alone (4.4 vs 2.6 years, P<0.001). Inclusion of normal PSA level as a criterion for disease-free survival also resulted in significantly increased median disease-free survival in patients receiving the combination therapy (2.7 vs 1.5 years, P<0.001).

14.2 Prostatic Carcinoma

In controlled studies of patients with advanced prostatic cancer comparing ZOLADEX to orchiectomy, the long-term endocrine responses and objective responses were similar between the two treatment arms. Additionally, duration of survival was similar between the two treatment arms in a comparative trial.

14.3 Endometriosis

In controlled clinical studies using the 3.6 mg formulation every 28 days for 6 months, ZOLADEX was shown to be as effective as danazol therapy in relieving clinical symptoms (dysmenorrhea, dyspareunia and pelvic pain) and signs (pelvic tenderness, pelvic induration) of endometriosis and decreasing the size of endometrial lesions as determined by laparoscopy. In one study comparing ZOLADEX with danazol (800 mg/day), 63% of ZOLADEX-treated patients and 42% of danazol-treated patients had a greater than or equal to 50% reduction in the extent of endometrial lesions. In the second study comparing ZOLADEX with danazol (600 mg/day), 62% of ZOLADEX-treated and 51% of danazol-treated patients had a greater than or equal to 50% reduction in the extent of endometrial lesions. The clinical significance of a decrease in endometriotic lesions is not known at this time; and in addition, laparoscopic staging of endometriosis does not necessarily correlate with severity of symptoms.

In these two studies, ZOLADEX led to amenorrhea in 92% and 80%, respectively, of all treated women within 8 weeks after initial administration. Menses usually resumed within 8 weeks following completion of therapy.

Within 4 weeks following initial administration, clinical symptoms were significantly reduced, and at the end of treatment were, on average, reduced by approximately 84%.

During the first two months of ZOLADEX use, some women experience vaginal bleeding of variable duration and intensity. In all likelihood, this bleeding represents estrogen withdrawal bleeding, and is expected to stop spontaneously.

There is insufficient evidence to determine whether pregnancy rates are enhanced or adversely affected by the use of ZOLADEX.

14.4 Endometrial Thinning

Two trials were conducted with ZOLADEX prior to endometrial ablation for dysfunctional uterine bleeding.

Trial 0022, was a double-blind, prospective, randomized, parallel-group multicenter trial conducted in 358 premenopausal women with dysfunctional uterine bleeding. Eligible patients were randomized to receive either two depots of ZOLADEX 3.6 mg (n=180) or two placebo injections (n=178) administered four weeks apart. One hundred seventy five patients in each group underwent endometrial ablation using either diathermy loop alone or in combination with rollerball approximately 2 weeks after the second injection. Endometrial thickness was assessed immediately before surgery using a transvaginal ultrasonic probe. The incidence of amenorrhea was compared between the ZOLADEX and placebo groups at 24 weeks after endometrial ablation.

The median endometrial thickness before surgery was significantly less in the ZOLADEX treatment group (1.50 mm) compared to the placebo group (3.55 mm). Six months after surgery, 40% of patients (70/175) treated with ZOLADEX in Trial 0022 reported amenorrhea as compared with 26% who had received placebo injections (44/171), a difference that was statistically significant.

Trial 0003, was a single center, open-label, randomized trial in premenopausal women with dysfunctional uterine bleeding. The trial allowed for a comparison of 1 depot of ZOLADEX and 2 depots of ZOLADEX administered 4 weeks apart with ablation using Nd: YAG laser occurring 4 weeks after ZOLADEX administration. Forty patients were randomized into each of the ZOLADEX treatment groups.

The median endometrial thickness before surgery was significantly less in the group treated with two depots (0.5 mm) compared to the group treated with one depot (1 mm). No difference in the incidence of amenorrhea was found at 24 weeks (24% in both groups). Of the 74 patients that completed the trial, 53% reported hypomenorrhea and 20% reported normal menses six months after surgery.

14.5 Breast Cancer

The Southwest Oncology Group conducted a prospective, randomized clinical trial (SWOG-8692 [INT-0075]) in premenopausal women with advanced estrogen receptor positive or progesterone receptor positive breast cancer which compared ZOLADEX with oophorectomy. On the basis of interim data from 124 women, the best objective response (CR+PR) for the ZOLADEX group is 22% versus 12% for the oophorectomy group. The median time to treatment failure is 6.7 months for patients treated with ZOLADEX and 5.5 months for patients treated with oophorectomy. The median survival time for the ZOLADEX arm is 33.2 months and for the oophorectomy arm is 33.6 months.

Subjective responses based on measures of pain control and performance status were observed with both treatments; 48% of the women in the ZOLADEX treatment group and 50% in the oophorectomy group had subjective responses. In the clinical trial (SWOG-8692 [INT–0075]), the mean post treatment estradiol level was reported as 17.8 pg/mL. (The mean estradiol level in post-menopausal women as reported in the literature is 13 pg/mL.) During the conduct of the clinical trial, women whose estradiol levels were not reduced to the postmenopausal range, received two ZOLADEX depots, thus, increasing the dose of ZOLADEX from 3.6 mg to 7.2 mg.

Findings were similar in uncontrolled clinical trials involving patients with hormone receptor positive and negative breast cancer. Premenopausal women with estrogen receptor (ER) status of positive, negative, or unknown participated in the uncontrolled (Phase II and Trial 2302) clinical trials. Objective tumor responses were seen regardless of ER status, as shown in the following table.

Table 8 OBJECTIVE RESPONSE BY ER STATUS
 | CR + PR/Total No. (%)
ER Status | Phase II (N=228) | Trial 2302 (N=159)
Positive | 43/119 (36) | 31/86 (36)
Negative | 6/33 (18) | 3/26 (10)
Unknown | 20/76 (26) | 18/44 (41)

16 HOW SUPPLIED/STORAGE AND HANDLING

ZOLADEX is supplied as a sterile and totally biodegradable D,L-lactic and glycolic acids copolymer impregnated with 3.8 mg goserelin acetate, equivalent to 3.6 mg of goserelin, in a disposable syringe device fitted with a 16-gauge x 36 +/- 0.5 mm siliconized hypodermic needle with protective needle sleeve [SafeSystem® Syringe] (NDC 70720-950-36). The unit is sterile and comes in a sealed, light- and moisture-proof, aluminum foil laminate pouch containing a desiccant capsule. Store at room temperature (do not exceed 25°C [77°F]).

17 PATIENT COUNSELING INFORMATION

17.1 Severe Cutaneous Adverse Reactions

Inform patients that severe cutaneous adverse reactions (SCARs), including Stevens-Johnson syndrome (SJS), toxic epidermal necrolysis (TEN), drug reaction with eosinophilia and systemic symptoms (DRESS), and acute generalized exanthematous pustulosis (AGEP), which may be life threatening or fatal, may occur during treatment with ZOLADEX. Advise patients to contact their healthcare provider or seek medical attention right away if they experience signs or symptoms of SCARs, e.g., a prodrome of fever, flu-like symptoms, mucosal lesions, progressive skin rash, or lymphadenopathy [see Warnings and Precautions (5.7) and Adverse Reactions (6.10)].

17.2 Males

The use of ZOLADEX in patients at particular risk of developing ureteral obstruction or spinal cord compression should be considered carefully and the patients monitored closely during the first month of therapy. Patients with ureteral obstruction or spinal cord compression should have appropriate treatment prior to initiation of ZOLADEX therapy [see Warnings and Precautions (5.2) and Adverse Reactions (6.2)].

The use of GnRH agonists may cause a reduction in bone mineral density. In men, data suggest the use of a bisphosphonate in combination with a GnRH agonist may reduce bone mineral loss [see Adverse Reactions (6.8) and (6.10)].

Patients should be informed that diabetes or loss of glycemic control in patients with pre-existing diabetes has been reported during treatment with GnRH agonists, including ZOLADEX. Therefore, consideration should be given to monitoring blood glucose and/or glycosylated hemoglobin (HbA1c) periodically in patients receiving ZOLADEX [see Warnings and Precautions (5.3)].

A small increased risk of developing myocardial infarction, sudden cardiac death and stroke has been reported in association with use of GnRH agonists in men. Patients receiving a GnRH agonist should be monitored for symptoms and signs suggestive of development of cardiovascular disease and be managed according to current clinical practice [see Warnings and Precautions (5.4)].

Injection site injury has been reported following injection of ZOLADEX. Inform patients to contact their doctor immediately if they experience any of the following symptoms: abdominal pain, abdominal distension, dyspnea, dizziness, hypotension and/or any altered levels of consciousness [see Warnings and Precautions (5.10)].

17.3 Females

1. Menstruation should stop with effective doses of ZOLADEX. The patient should notify her physician if regular menstruation persists. Patients missing one or more successive doses of ZOLADEX may experience breakthrough menstrual bleeding [see Warnings and Precautions (5.1)].
2. ZOLADEX should not be used in a pregnant or breastfeeding woman except for the palliative treatment of advanced breast cancer. ZOLADEX may harm the fetus and increase the risk for pregnancy loss [see Contraindications (4.2), Warnings and Precautions (5.1) and Use in Specific Populations (8.1)].
3. A woman should not begin ZOLADEX treatment if she has undiagnosed abnormal vaginal bleeding, or is allergic to any of the components of ZOLADEX [see Clinical Studies (14.3)].
4. Premenopausal women using ZOLADEX must use nonhormonal contraception during treatment and for 12 weeks after treatment ends [see Warnings and Precautions (5.1)].
5. If a patient becomes pregnant while using ZOLADEX for endometriosis or endometrial thinning, ZOLADEX treatment should be discontinued. The patient should be advised of the possible risks to the pregnancy and fetus, including an increased risk of pregnancy loss [see Contraindications (4.2) and Use in Specific Populations (8.1)].
6. Those adverse events occurring most frequently in clinical studies with ZOLADEX are associated with hypoestrogenism; of these, the most frequently reported are hot flashes (flushes), headaches, vaginal dryness, emotional lability, change in libido, depression, sweating and change in breast size. Inform patients that depression may occur or worsen during treatment with GnRH agonists, including ZOLADEX, especially in patients with a history of depression. Advise patients to immediately report thoughts and behaviors of concern to healthcare providers [see Warnings and Precautions (5.10)]. Clinical studies in endometriosis suggest the addition of Hormone Replacement Therapy (estrogens and/or progestins) to ZOLADEX may decrease the occurrence of vasomotor symptoms and vaginal dryness associated with hypoestrogenism without compromising the efficacy of ZOLADEX in relieving pelvic symptoms. The optimal drugs, dose and duration of treatment has not been established [see Dosage and Administration (2.3) and Adverse Reactions (6.5) and (6.7)].
7. The use of GnRH agonists in women may cause a reduction in bone mineral density. In women, current available data suggest that recovery of bone loss occurs on cessation of therapy in the majority of patients.
  In patients with a history of prior treatment that may have resulted in bone mineral density loss and/or in patients with major risk factors for decreased bone mineral density such as chronic alcohol abuse and/or tobacco abuse, significant family history of osteoporosis, or chronic use of drugs that can reduce bone density such as anticonvulsants or corticosteroids, ZOLADEX therapy may pose an additional risk. In these patients the risks and benefits must be weighed carefully before therapy with ZOLADEX is instituted [see Adverse Reactions (6.8) and (6.10)].
8. Currently, there are no clinical data on the effects of retreatment or treatment of benign gynecological conditions with ZOLADEX for periods in excess of 6 months [see Dosage and Administration (2.3)].
9. As with other hormonal interventions that disrupt the pituitary-gonadal axis, some patients may have delayed return to menses. The rare patient, however, may experience persistent amenorrhea [see Drug Interactions (7.1) and Clinical Studies (14.3) and (14.4)].
10. Injection site injury has been reported following injection of ZOLADEX. Inform patients to contact their doctor immediately if they experience any of the following symptoms: abdominal pain, abdominal distension, dyspnea, dizziness, hypotension and/or any altered levels of consciousness [see Warnings and Precautions (5.10)].

ZOLADEX® and SAFESYSTEM® are registered trademarks of AstraZeneca or its affiliates and are used herein under license.

©2025 TerSera Therapeutics LLC

Distributed by: TerSera Therapeutics LLC, Deerfield, IL 60015

TerSera®
therapeutics

Principal Display Panel - Zoladex Carton Label

NDC 70720-950-36

Zoladex® 3.6mg

goserelin implant

3.6 mg goserelin
Equivalent to 3.8 mg goserelin acetate

One Single-Use Syringe
For Subcutaneous Injection